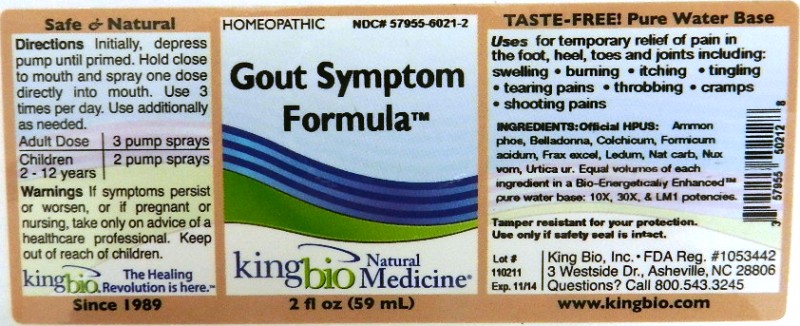 DRUG LABEL: Gout Symptom Formula
NDC: 57955-6021 | Form: LIQUID
Manufacturer: King Bio Inc.
Category: homeopathic | Type: HUMAN OTC DRUG LABEL
Date: 20111118

ACTIVE INGREDIENTS: AMMONIUM PHOSPHATE, DIBASIC 10 [hp_X]/59 mL; ATROPA BELLADONNA 10 [hp_X]/59 mL; COLCHICUM AUTUMNALE BULB 10 [hp_X]/59 mL; FORMIC ACID 10 [hp_X]/59 mL; FRAXINUS EXCELSIOR LEAF 10 [hp_X]/59 mL; LEDUM PALUSTRE TWIG 10 [hp_X]/59 mL; SODIUM CARBONATE 10 [hp_X]/59 mL; STRYCHNOS NUX-VOMICA SEED 10 [hp_X]/59 mL; URTICA URENS 10 [hp_X]/59 mL
INACTIVE INGREDIENTS: WATER

Gout Symptom Formula

Active Ingredients

Official HPUS

Ammonium Phosphoricum, Belladonna, Colchicum Autumnale, Formicum Acidum, Fraxinus Excelsior, Ledum Palustre, Natrum Carbonicum, Nux Vomica, and Urtica Urens.

Reference image gout.jpg

Inactive Ingredient

Equal volumes of each ingredient in a Bio-Energetically Enhanced pure water base. 10X, 30X, and LM1 potencies.
Reference image gout.jpg

Dosage and Administration

Directions Initially, depress pump until primed. Hold close to mouth and spray one dose directly into mouth. Use 3 times per day. Use additionally as needed.

Adult Dose: 3 pump sprays

Children: (2-12 years) 2 pump sprays

Reference image gout.jpg

Purpose

For Temporary relief of pain in the foot, heel, toes and joints including: swelling, burning, itching, tingling, tearing pains, throbbing, cramps, shooting pains.

Reference image gout.jpg

Warnings

If symptoms persist or worsen, or if pregnant or nursing, take only on advice of a healthcare professional. Keep out of reach of children.

Other: Tamper resistant for your protection. Use only if safety seal is intact.

Reference image gout.jpg

Keep out of reach of children.

Reference image gout.jpg

Indications and Usage

Uses for temporary relief of pain in the foot, heel, toes and joints including:

- swelling
- burning
- itching
- tingling
- tearing pains
- throbbing
- cramps
- shooting pains

Reference image gout.jpg

PACKAGE LABEL

King Bio Inc.

3 Westside Drive

Asheville, NC 28806

www.kingbio.com

Questions? Call 800.543.3245